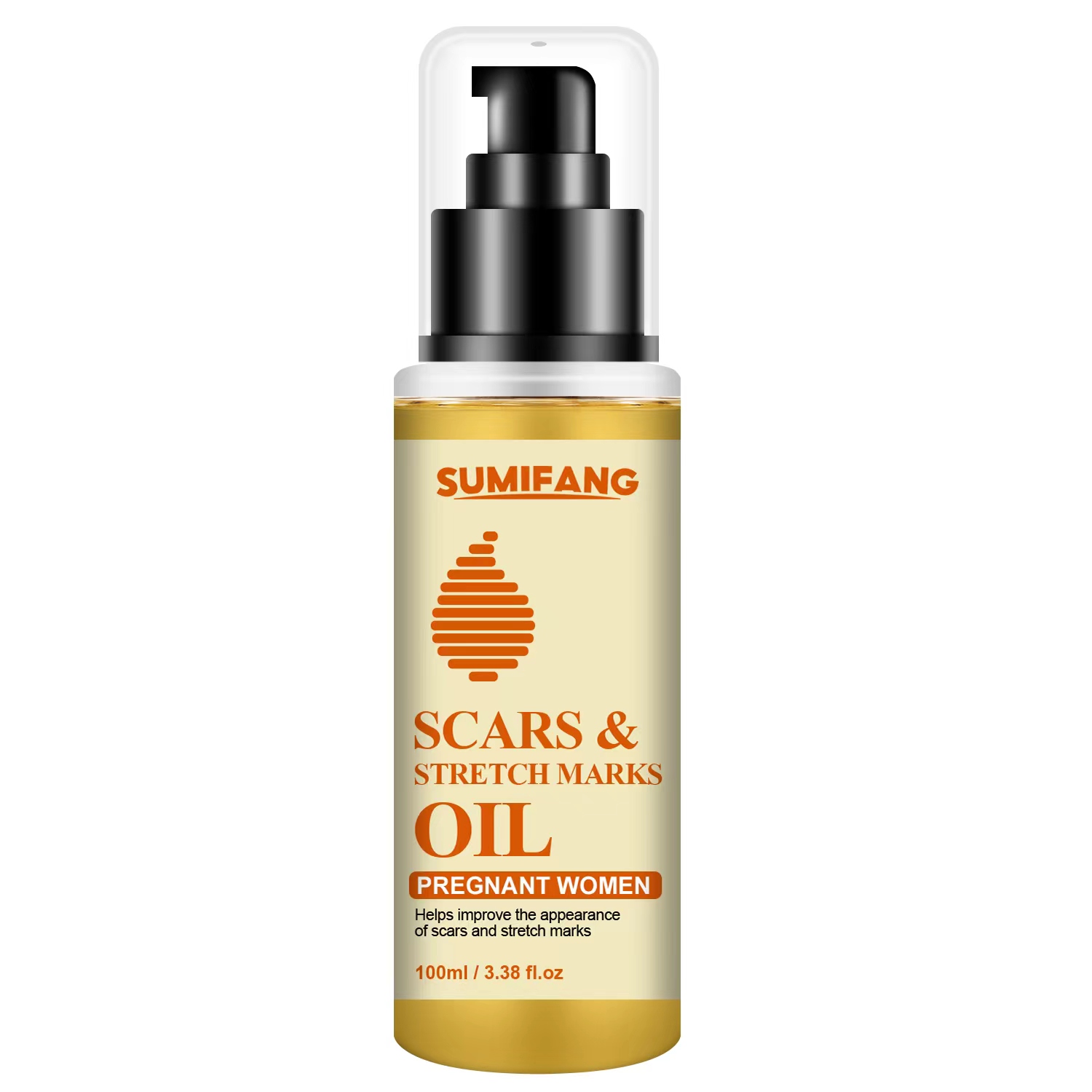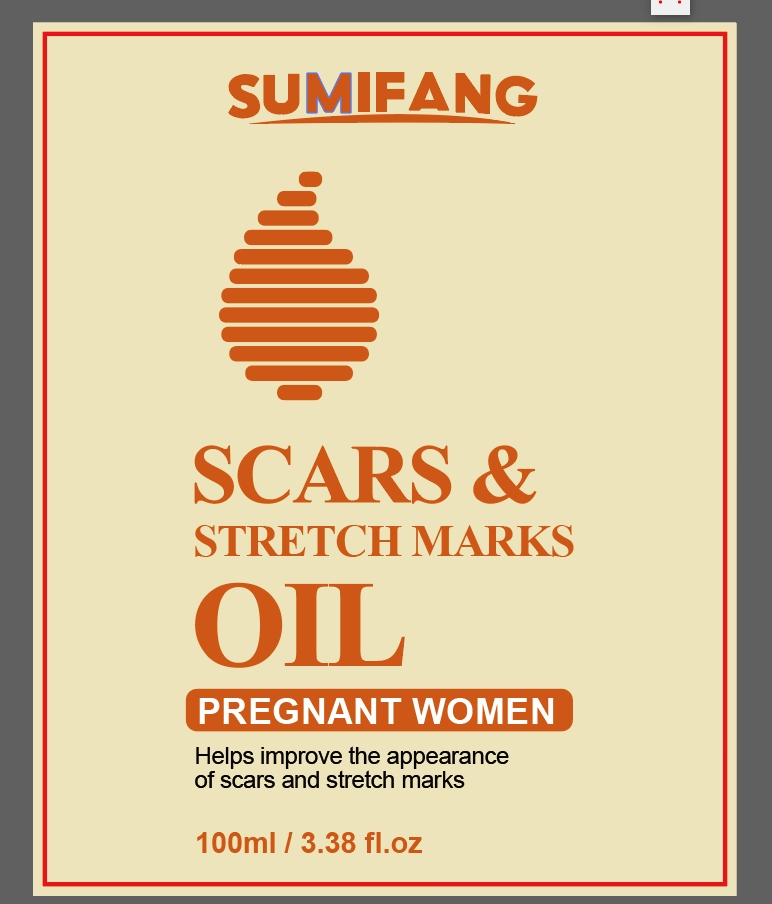 DRUG LABEL: BODY OlL
NDC: 84025-062 | Form: LIQUID
Manufacturer: Guangzhou Yanxi Biotechnology Co., Ltd
Category: otc | Type: HUMAN OTC DRUG LABEL
Date: 20240711

ACTIVE INGREDIENTS: 1,2-BUTANEDIOL 3 mg/100 mL; ALLANTOIN 2 mg/100 mL
INACTIVE INGREDIENTS: WATER

DOSAGE AND ADMINISTRATION

As a general medicine

WARNINGS

Keep out of Children

INACTIVE INGREDIENT

Aqua

INDICATIONS AND USAGE

As a general medicine

Keep out of Children

PURPOSE

repair scars